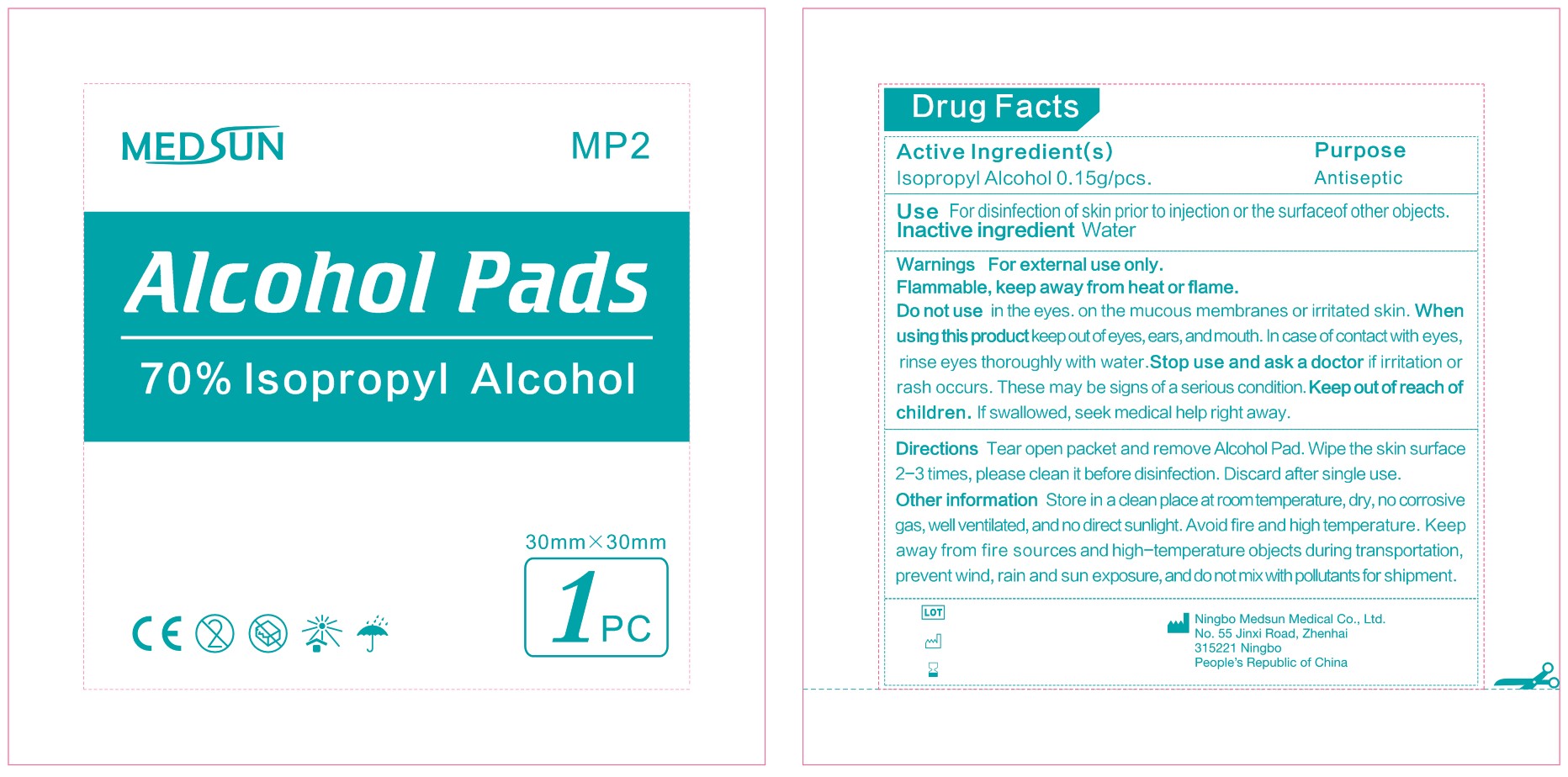 DRUG LABEL: Alcohol Pads
NDC: 80558-002 | Form: SWAB
Manufacturer: Ningbo Medsun Medical Co., Ltd.
Category: otc | Type: HUMAN OTC DRUG LABEL
Date: 20200918

ACTIVE INGREDIENTS: ISOPROPYL ALCOHOL 0.7 1/1 1
INACTIVE INGREDIENTS: WATER

Active Ingredient(s)

Isopropyl Alcohol 0.15g/pcs.

Purpose

Antiseptic

Use

For disinfection of skin prior to injection or the surface of other objects.

Warnings

For external use only.

Flammable, keep away from heat or flame.

Do not use

- in the eyes
- on the mucous membranes or irritated skin

When using this product keep out of eyes, ears, and mouth. In case of contact with eyes, rinse eyes thoroughly with water.

Stop use and ask a doctor if irritation or rash occurs. These may be signs of a serious condition.

Keep out of reach of children. If swallowed, seek medical help right away.

Directions

- Tear open packet and remove Alcohol Pad.
- Wipe the skin surface 2-3 times, please clean it before disinfection.
- Discard after single use.

Other information

- Store in a clean place at room temperature, dry, no corrosive gas, well ventilated, and no direct sunlight. Avoid fire and high temperature.
- Keep away from fire sources and high-temperature objects during transportation, prevent wind, rain and sun exposure, and do not mix with pollutants for shipment.

Inactive ingredient

Water

Package Label - Principal Display Panel

Isopropyl Alcohol 0.15g/pcs. NDC: 80558-002-01